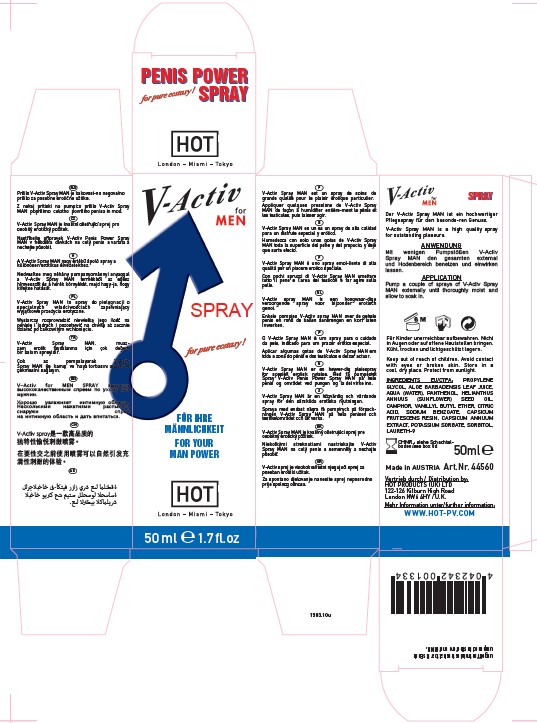 DRUG LABEL: V-ACTIV FOR MEN
NDC: 71326-204 | Form: SPRAY
Manufacturer: HOT PRODUCTIONS AND VERTRIEBS GMBH
Category: homeopathic | Type: HUMAN OTC DRUG LABEL
Date: 20231005

ACTIVE INGREDIENTS: CAPSICUM ANNUUM WHOLE 0.1 g/100 mL; CAPSICUM FRUTESCENS WHOLE 0.1 g/100 mL
INACTIVE INGREDIENTS: ALOE VERA LEAF; PROPYLENE GLYCOL; PANTHENOL; CAMPHOR OIL; CETOSTEARYL ALCOHOL; VANILLYL BUTYL ETHER; ANHYDROUS CITRIC ACID; GLYCERIN; SUNFLOWER OIL; SODIUM BENZOATE; POTASSIUM SORBATE; POLIDOCANOL; WATER; SORBITOL

HOT PRODUCTS - V-ACTIV FOR MEN SPRAY (71326-204)

ACTIVE INGREDIENTS

CAPSISUM FRUTESCENS 0.1X HPUS

CAPSICUM ANNUUM EXTRACT 0.1X HPUS

PURPOSE

Topical Anesthetic

USE

V-Activ penis power spray is a highquality treatment spray for special erotic enjoyment. Apply the spray just prior to sexual intercourse for a spontaneously lust-full experience.

WARNINGS

Do not allow it to contact the eyes or areas of open skin.
Do not use during pregnancy!

Keep out of reach of children.

DIRECTIONS

pump the V-Activ penis power spray a few times to moisten the entire penis and testes area and allow it to take effect.
Wait approx. 2-3 minutes for the spray to be completely absorbed before putting on a condom.

OTHER INFORMATION

- Store in a cool, dry place. Protect from sunlight.

INACTIVE INGREDIENTS

PROPYLENE GLYCOL, ALOE BARBADENSIS LEAF JUICE, AQUA, PANTHENOL, HELIANTHUS ANNUUS (SUNFLOWER) SEED OIL, CAMPHOR, VANILLYL BUTYL ETHER, CITRIC ACID, SODIUM BENZOATE, CAPSICUM FRUTESCENS RESIN, CAPSICUM ANNUUM EXTRACT, POTASSIUM SORBATE, SORBITOL, LAURETH-9